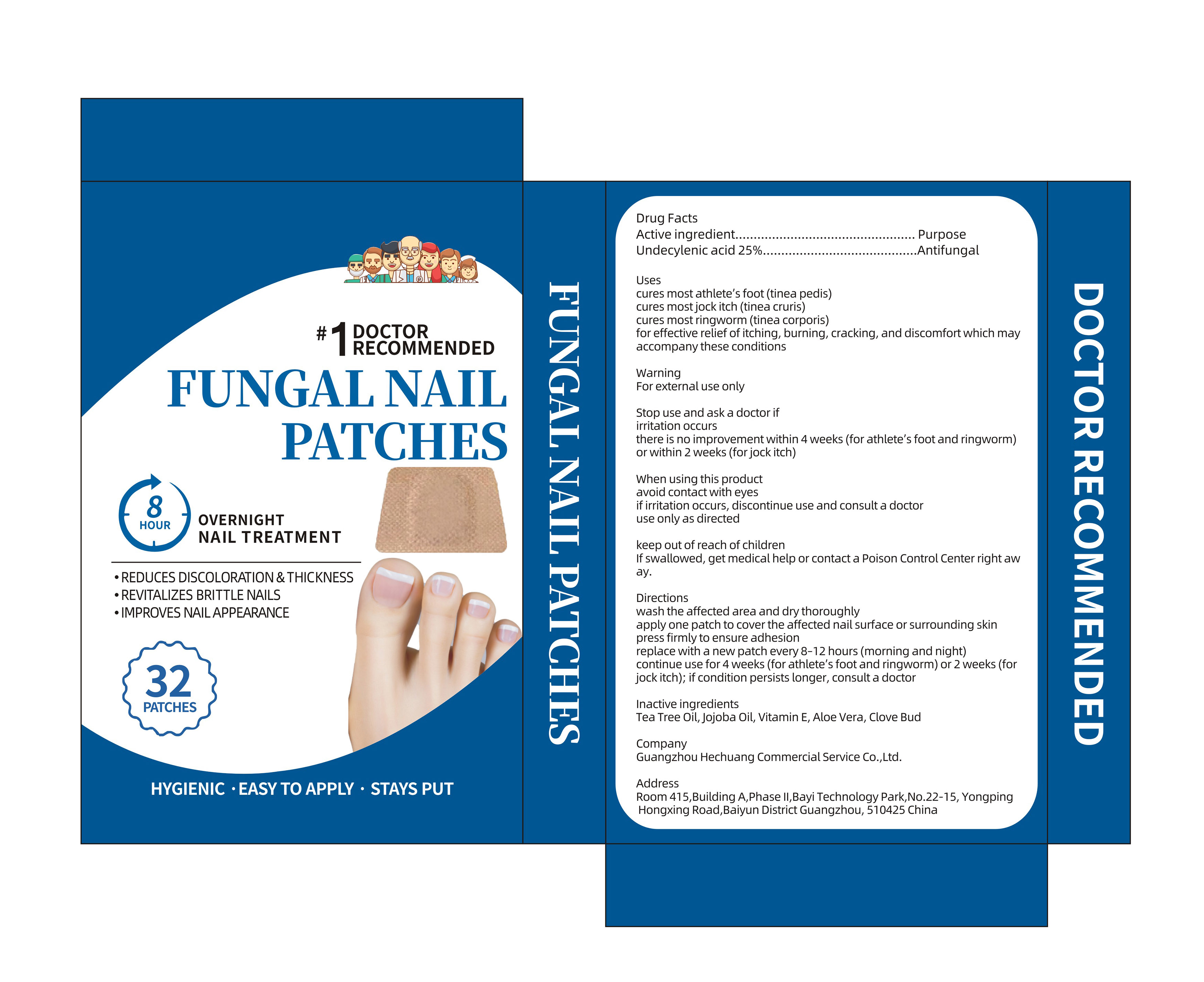 DRUG LABEL: FUNGAL NAIL PATCHES
NDC: 87298-013 | Form: PATCH
Manufacturer: Guangzhou Hechuang Commercial Service Co.,Ltd.
Category: otc | Type: HUMAN OTC DRUG LABEL
Date: 20260103

ACTIVE INGREDIENTS: UNDECYLENIC ACID 25 g/100 g
INACTIVE INGREDIENTS: JOJOBA OIL; ALOE VERA LEAF; SYZYGIUM AROMATICUM FRUIT; VITAMIN E POLYETHYLENE GLYCOL SUCCINATE; TEA TREE OIL

Active ingredient

Undecylenic acid 25%

Purpose

Antifungal

Inactive ingredients

Tea Tree Oil, Jojoba Oil, Vitamin E, Aloe Vera, Clove Bud

Uses

cures most athlete's foot (tinea pedis)
cures most jock itch (tinea cruris)
cures most ringworm (tinea corporis)
for effective relief of itching,burning,cracking,and discomfort which may accompany these conditions

Directions

wash the affected area and dry thoroughly apply one patch to cover the affected nail surface or surrounding skin press firmly to ensure adhesion replace with a new patch every 8-12 hours (morning and night) continue use for 4 weeks (for athlete's foot and ringworm) or 2 weeks (for jock itch); if condition persists longer, consult a doctor

When using this product

avoid contact with eyes
if irritation occurs,discontinue use and consult a doctor use only as directed

Directions

wash the affected area and dry thoroughly apply one patch to cover the affected nail surface or surrounding skin press firmly to ensure adhesion replace with a new patch every 8-12 hours (morning and night) continue use for 4 weeks (for athlete's foot and ringworm) or 2 weeks (for jock itch); if condition persists longer, consult a doctor

Stop use and ask a doctor if
irritation occurs
there is no improvement within 4 weeks(for athlete's foot and ringworm)
or within 2 weeks(for jock itch)

keep out of reach of children

If swallowed,get medical help or contact a Poison Control Center right away.

Warning

For external use only